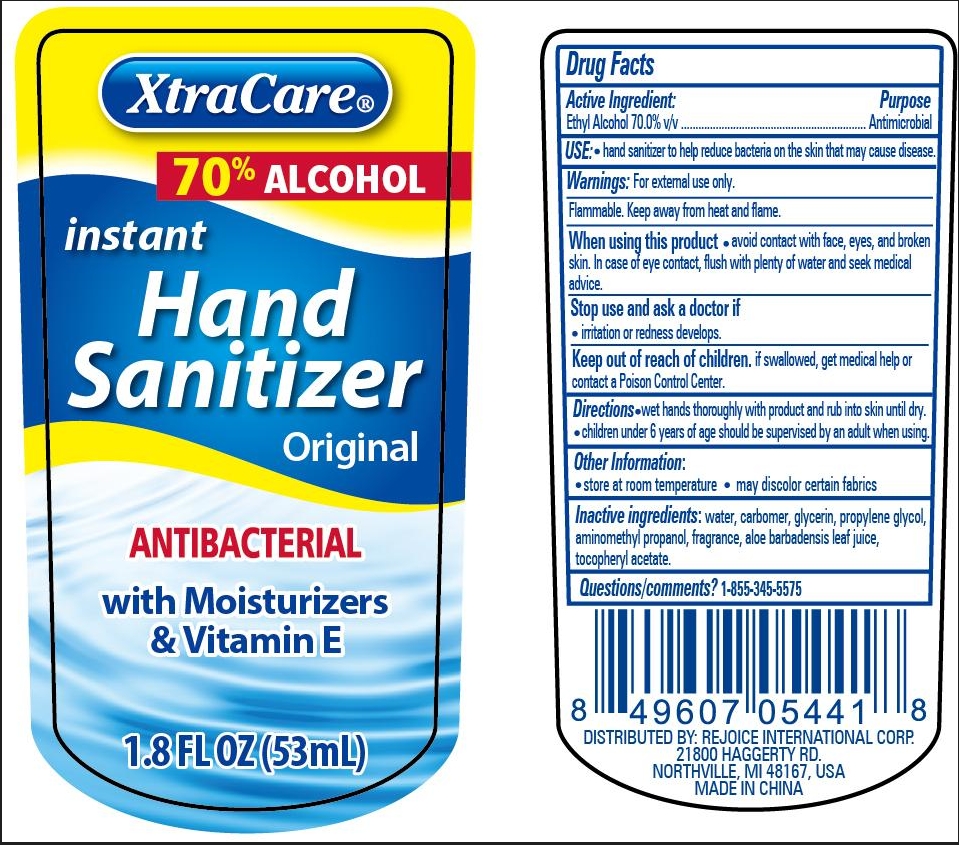 DRUG LABEL: Hand sanitizer 1.8oz with extra clip original
NDC: 75742-026 | Form: GEL
Manufacturer: Zhejiang Guoyao Jingyue Aerosol Co., Ltd.
Category: otc | Type: HUMAN OTC DRUG LABEL
Date: 20231004

ACTIVE INGREDIENTS: ALCOHOL 70 mL/100 mL
INACTIVE INGREDIENTS: AMINOMETHYLPROPANOL; .ALPHA.-TOCOPHEROL ACETATE; WATER; CARBOMER HOMOPOLYMER, UNSPECIFIED TYPE; GLYCERIN; PROPYLENE GLYCOL; ALOE VERA LEAF

Active Ingredients

Ethyl Alcohol 70.0% v/v

Purpose

Antimicrobial

Use

hand sanitizer to help reduce bacteria on the skin that may cause diease.

Warnings

For external use only

Flammable. Keep away from heat and flame.

When using this product

avoid contact with face, eyes, and broken skin. In case of eye contact, flush with plenty of water and seek medical advice.

Stop use and ask a doctor if

- irritation or redness develops

Keep out if reach of children

- if swallowed, get medical help or contact a Poison Control Center.

Directions

- wet hands thoroughly with product and rub into skin until dry.
- children under 6 years of age should be supervised by an adult when using.

Other information

- store at room temperature
- may discolor certain fabrics

Inactive ingredients

water

carbomer

glycerin

propylene glycol

aminomethyl propanol

fragrance

aloe barbadensis leaf juice

tocopheryl acetate